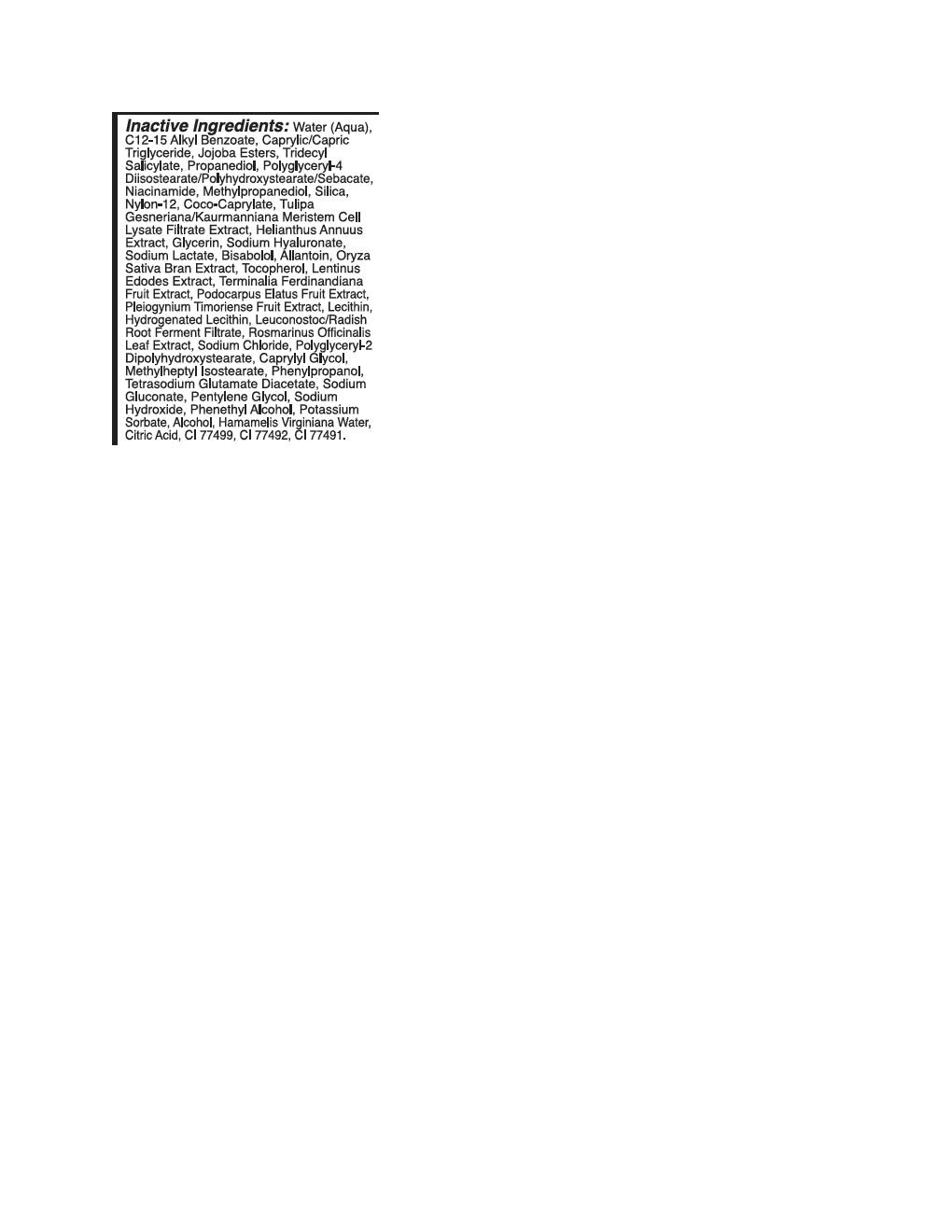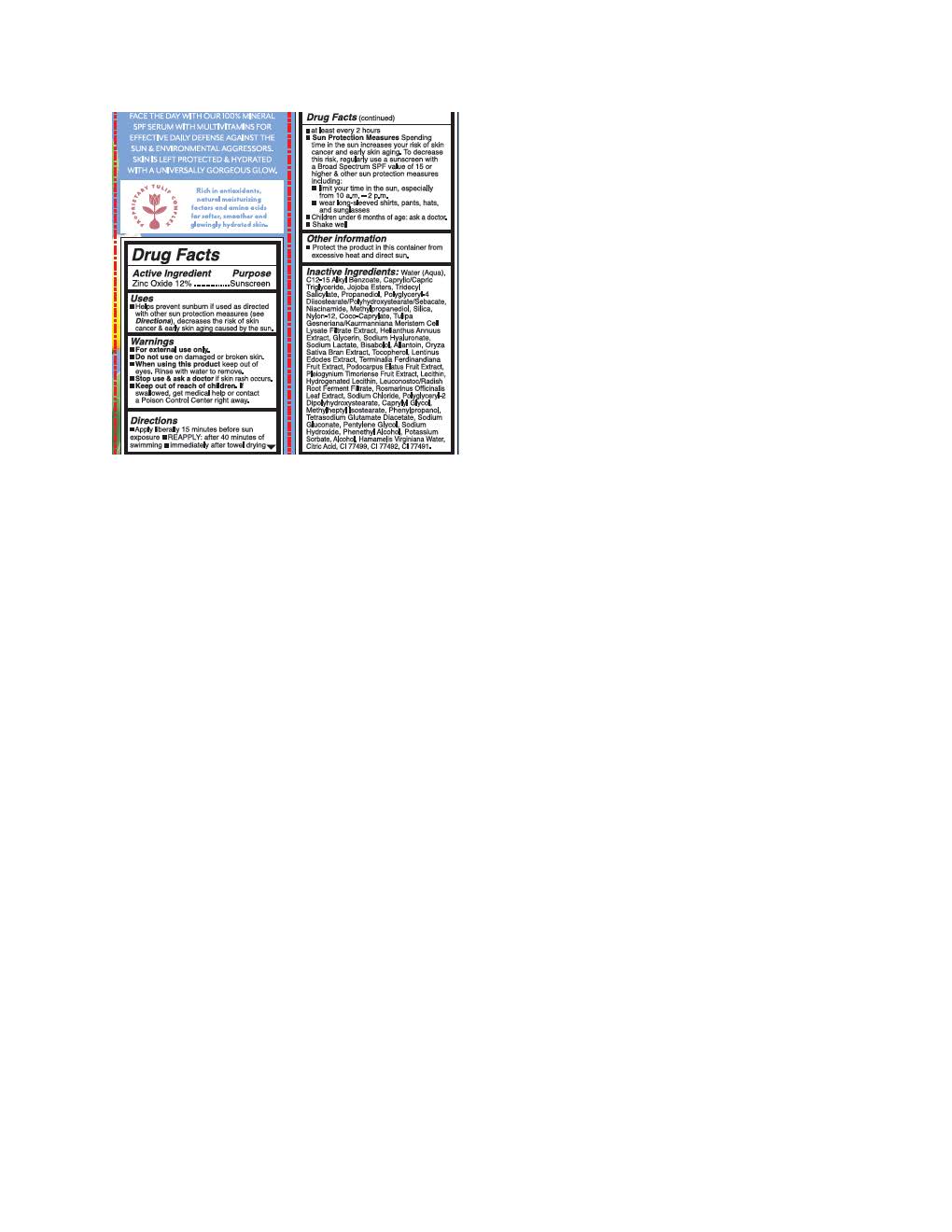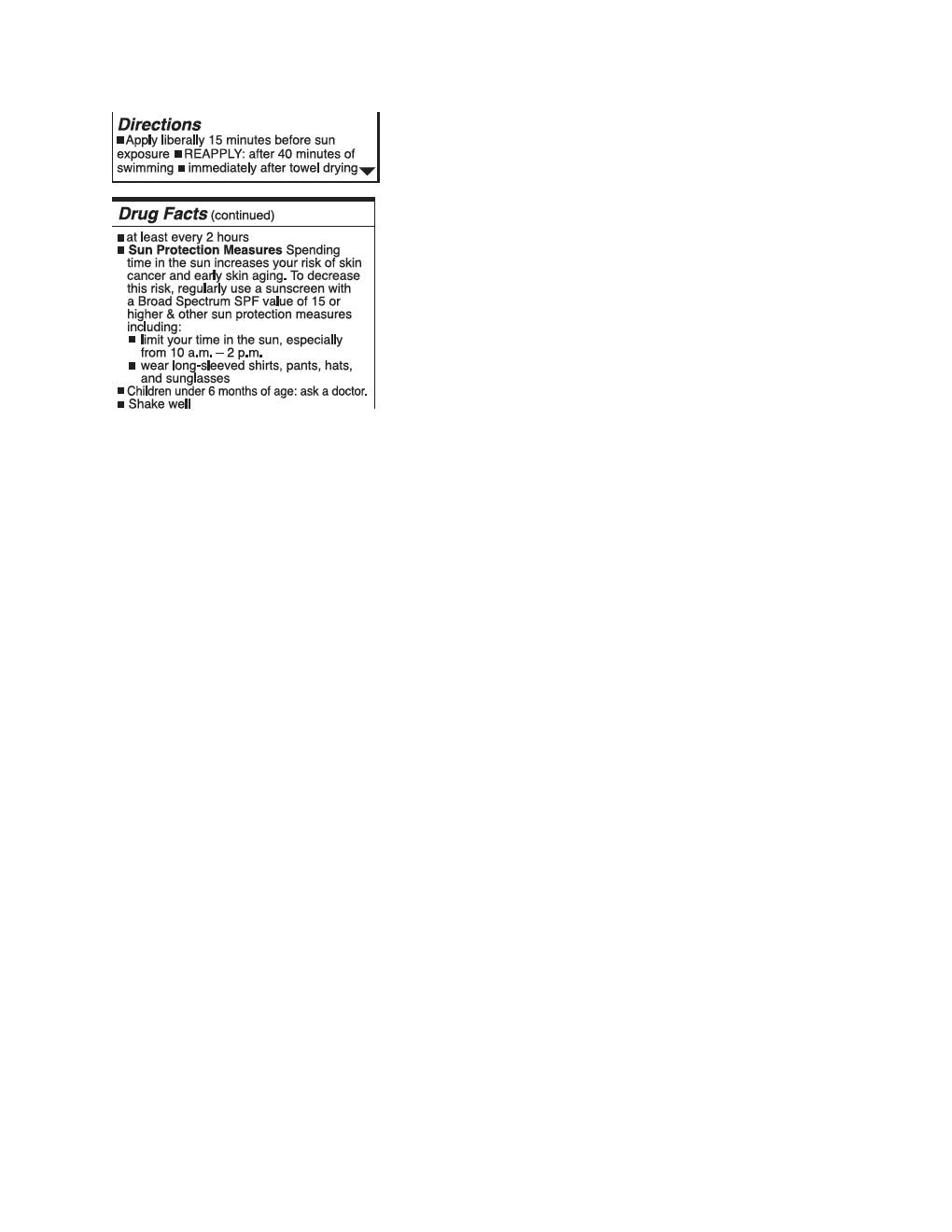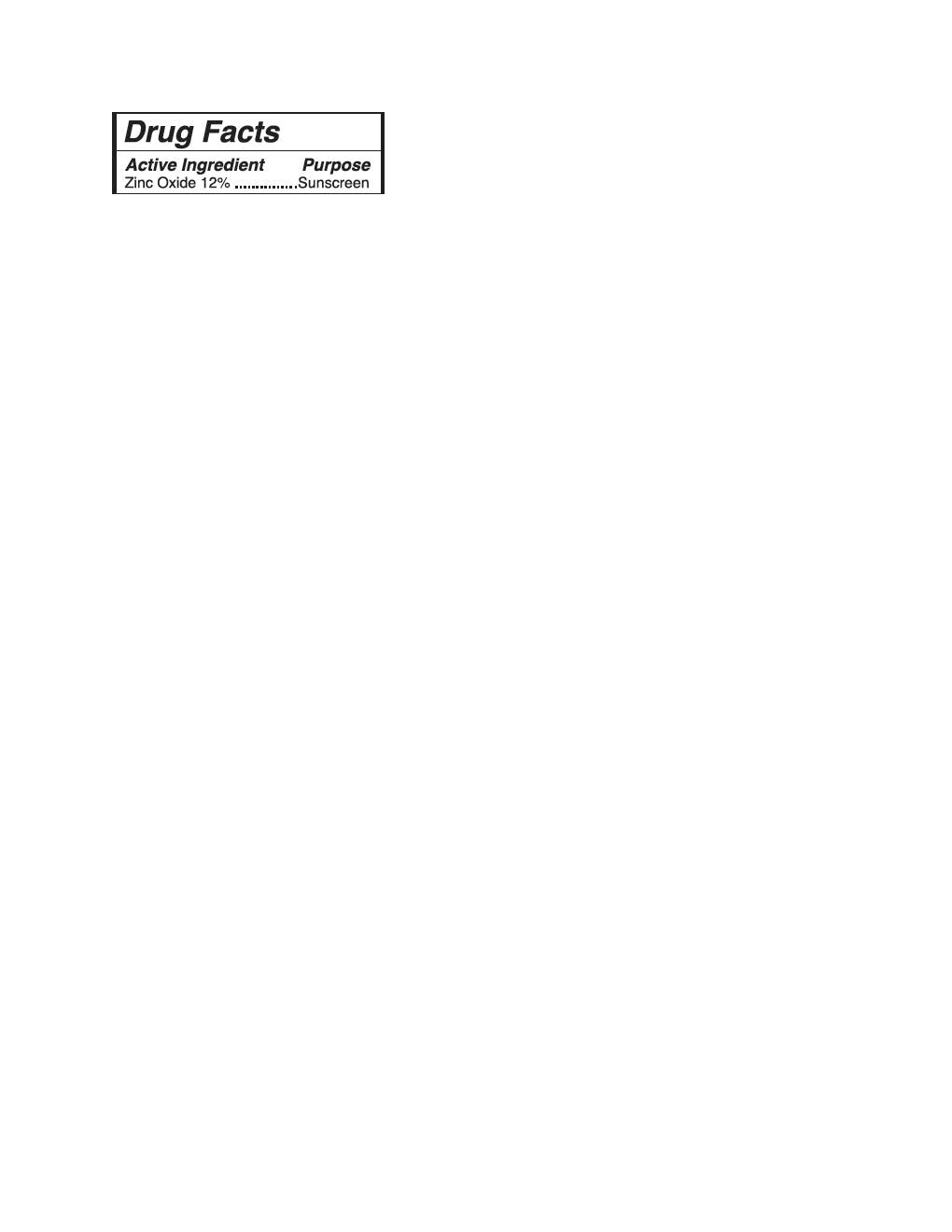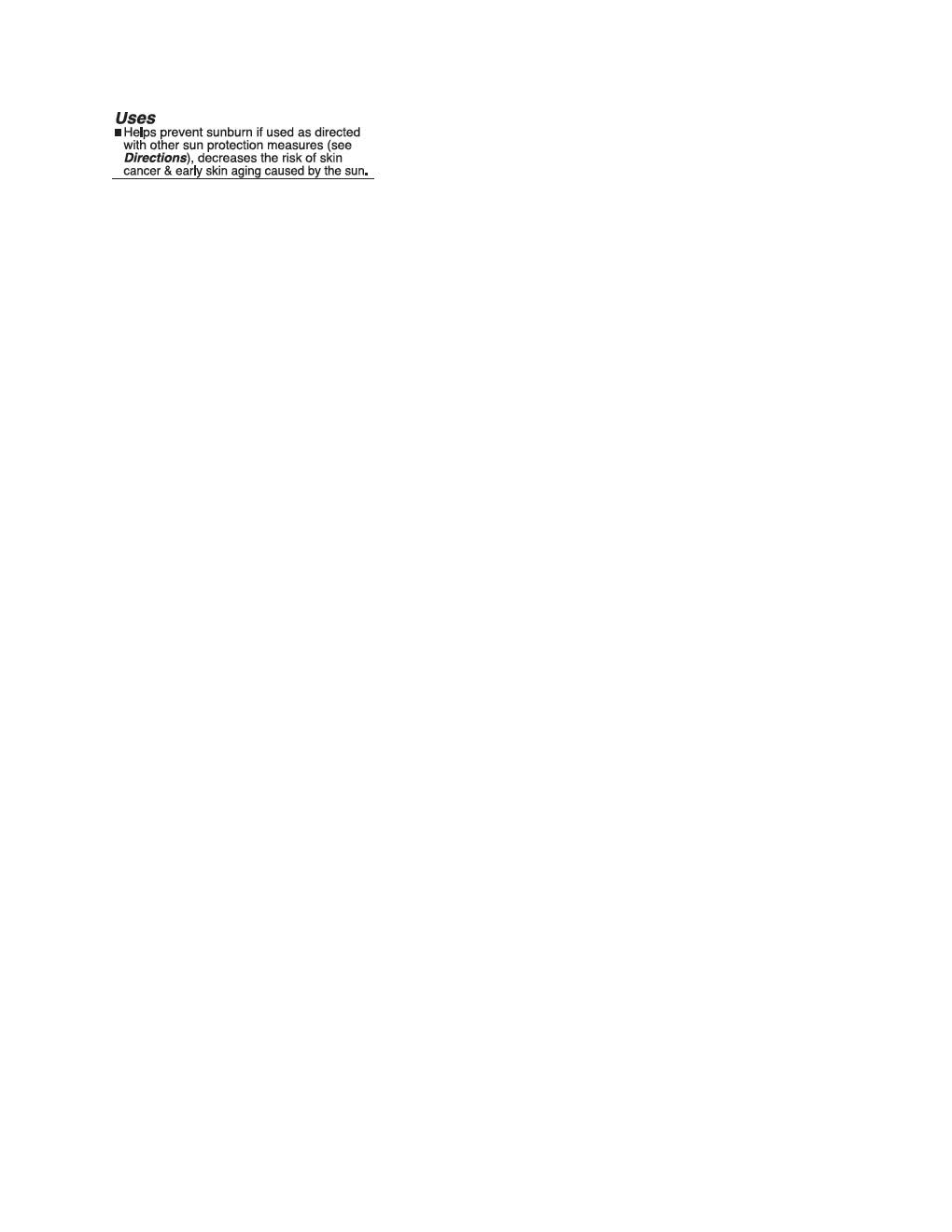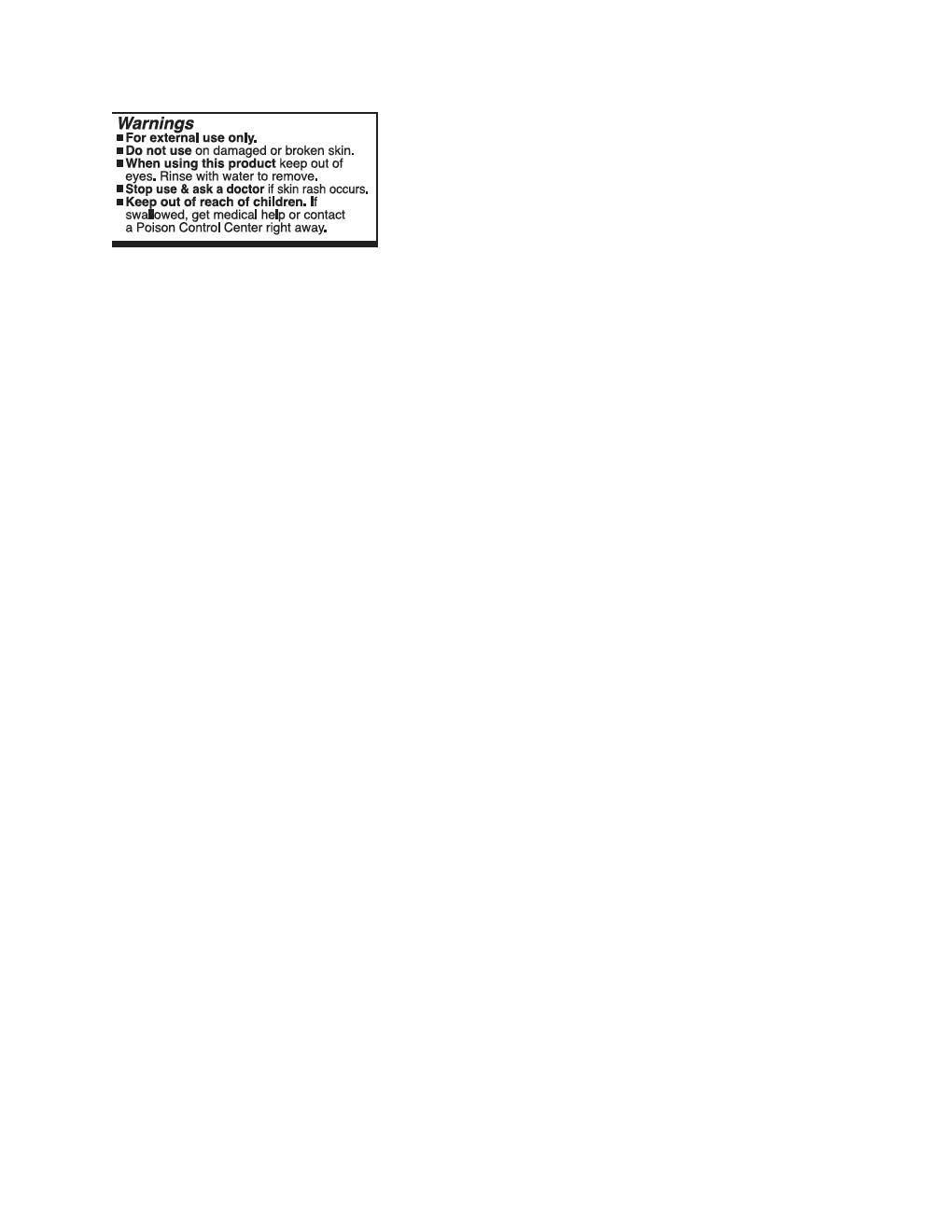 DRUG LABEL: Bloomeffects Tulip Dew
NDC: 82548-2193 | Form: LOTION
Manufacturer: Bloomeffects
Category: otc | Type: HUMAN OTC DRUG LABEL
Date: 20251010

ACTIVE INGREDIENTS: ZINC OXIDE 132 mg/1 mL
INACTIVE INGREDIENTS: JOJOBA OIL; ORYZA SATIVA WHOLE; TRIDECYL SALICYLATE; SILICON DIOXIDE; TOCOPHEROL; CAPRYLYL GLYCOL; COCO-CAPRYLATE; NYLON-12; PHENYLPROPANOL; FERRIC OXIDE RED; FERRIC OXIDE YELLOW; HELIANTHUS ANNUUS FLOWERING TOP; LECITHIN, SOYBEAN; METHYLHEPTYL ISOSTEARATE; METHYLPROPANEDIOL; POLYGLYCERYL-2 DIPOLYHYDROXYSTEARATE; ALLANTOIN; ALKYL (C12-15) BENZOATE; ROSMARINUS OFFICINALIS FLOWER; .ALPHA.-BISABOLOL, (+)-; SODIUM HYDROXIDE; WATER; NIACINAMIDE; PROPANEDIOL; TETRASODIUM GLUTAMATE DIACETATE; SODIUM CHLORIDE; POLYGLYCERYL-3 DIISOSTEARATE; PODOCARPUS ELATUS FRUIT; STEARALKONIUM HECTORITE; HAMAMELIS VIRGINIANA TOP WATER; LEUCONOSTOC/RADISH ROOT FERMENT FILTRATE; PENTYLENE GLYCOL; POTASSIUM SORBATE; FERROSOFERRIC OXIDE; SODIUM LACTATE; POLYGLYCERYL-4 DIISOSTEARATE/POLYHYDROXYSTEARATE/SEBACATE; SODIUM GLUCONATE

Bloomeffects Tulip Dew